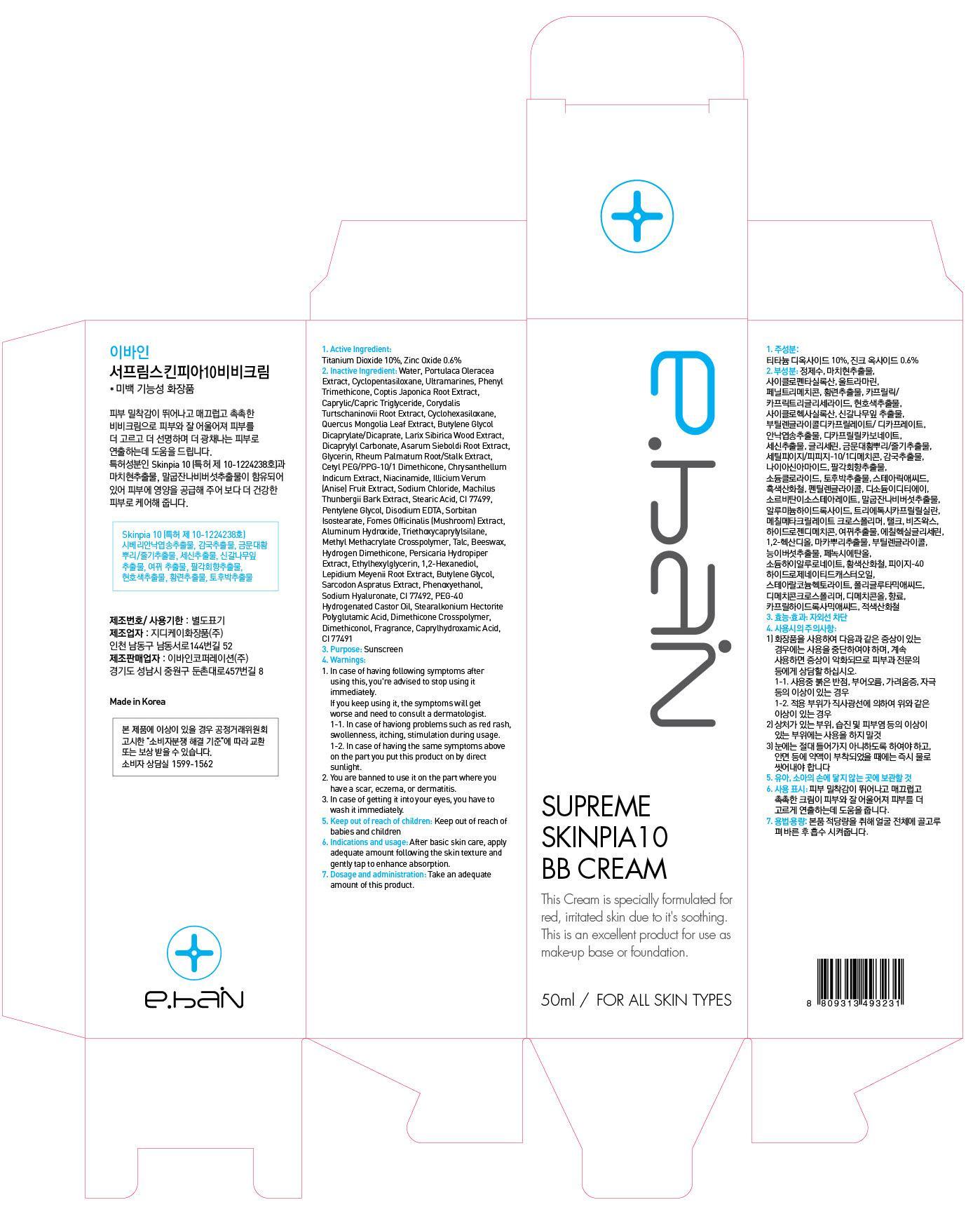 DRUG LABEL: SUPREME SKINPIA 10 BB
NDC: 62242-020 | Form: CREAM
Manufacturer: EBAIN Corporation Co., Ltd.
Category: otc | Type: HUMAN OTC DRUG LABEL
Date: 20140304

ACTIVE INGREDIENTS: Titanium Dioxide 5 mg/50 mL; Zinc Oxide 0.3 mg/50 mL
INACTIVE INGREDIENTS: Water; Phenyl Trimethicone

ACTIVE INGREDIENT

Active Ingredients: Titanium Dioxide 10%, Zinc Oxide 0.6%

INACTIVE INGREDIENT

Inactive Ingredients:
Water, Cyclopentasiloxane, Phenyl Trimethicone, Caprylic/Capric Triglyceride, Cyclohexasiloxane, Butylene Glycol Dicaprylate/Dicaprate, Dicaprylyl Carbonate, Glycerin, Cetyl PEG/PPG-10/1 Dimethicone, Niacinamide, Sodium Chloride, Stearic Acid, Pentylene Glycol,
Sorbitan Isostearate, Aluminum Hydroxide, Methyl Methacrylate Crosspolymer, Beeswax, Persicaria Hydropiper Extract, 1,2-Hexanediol, Butylene Glycol, Phenoxyethanol, CI 77492, Stearalkonium Hectorite, Dimethicone Crosspolymer, Dimethiconol, Fragrance, Caprylhydroxamic Acid, CI 77491, Portulaca Oleracea Extract, Ultramarines, Coptis Japonica Root Extract, Corydalis Turtschaninovii Root Extract, Quercus Mongolia Leaf Extract, Larix Sibirica Wood Extract, Asarum Sieboldi Root Extract, Rheum Palmatum Root/Stalk Extract, Chrysanthellum Indicum Extract, Illicium Verum (Anise) Fruit Extract, Machilus Thunbergii Bark Extract, CI 77499, Disodium EDTA, Fomes Officinalis (Mushroom) Extract, Triethoxycaprylylsilane, Talc, Hydrogen Dimethicone, Ethylhexylglycerin, Lepidium Meyenii Root Extract,
Sarcodon Aspratus Extract, Sodium Hyaluronate, PEG-40 Hydrogenated Castor Oil, Polyglutamic Acid

PURPOSE

Purpose: Sunscreen

WARNINGS

1. In case of having following symptoms after using this, you're advised to stop using it immediately.
If you keep using it, the symptoms will get worse and need to consult a dermatologist.
- In case of haviong problems such as red rash, swollenness, itching, stimulation during usage.
- In case of having the same symptoms above on the part you put this product on by direct sunlight.
2. You are banned to use it on the part where you have a scar, eczema, or dermatitis.
3. In case of getting it into your eyes, you have to wash it immediately.

Keep out of reach of children: Keep out of reach of babies and children

Indications and usage: After basic skin care, apply adequate amount following the skin texture and gently tap to enhance absorption.

Dosage and administration: Take an adequate amount of this product.